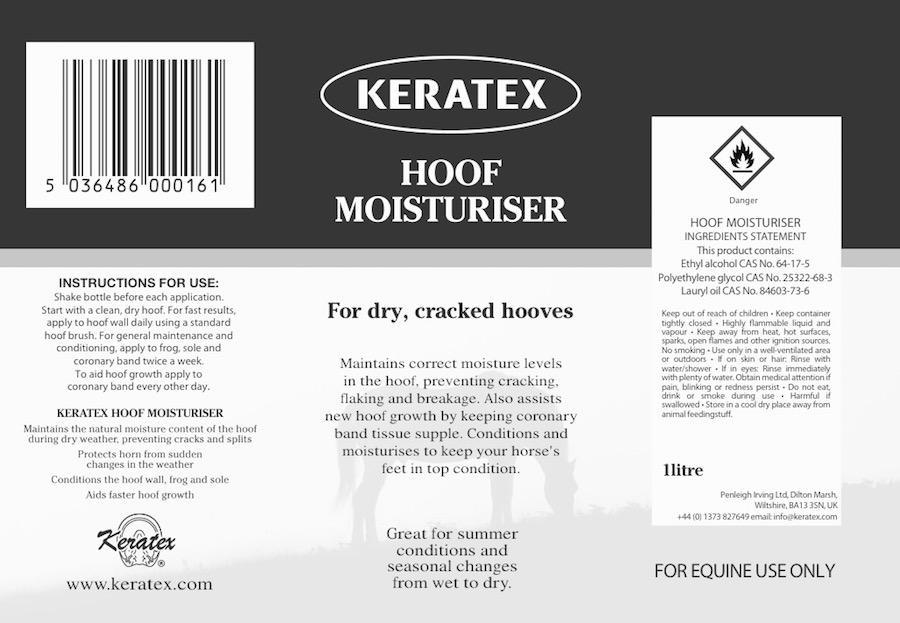 DRUG LABEL: Keratex
NDC: 27426-017 | Form: LIQUID
Manufacturer: Penleigh Irving Ltd
Category: animal | Type: OTC ANIMAL DRUG LABEL
Date: 20150709

ACTIVE INGREDIENTS: POLYETHYLENE GLYCOLS 167.5 mg/1.675 L; ALCOHOL 1506.83 mL/1.675 L; BAY LEAF OIL 0.67 mg/1.675 L

PACKAGE LABEL

Keratex Hoof Moisturiser

For dry, cracked hooves

Maintains correct moisture levels in the hoof, preventing cracking, flaking and breakage. Also assists new hoof growth by keeping the coronary band tissue supple. Conditions and moisturizes the keep your horse’s feet in top condition.

Great for summer conditions and seasonal changes from wet to dry.

Keratex Hoof Moisturiser maintains the natural moisture content of the hoof during dry weather, preventing cracks and splits. Protects horn from sudden changes in the weather. Conditions the hoof wall, frog and sole. Aids faster hoof growth.

Instructions for use: Shake bottle before each application. Start with clean, dry hoof. For fast results, apply to hoof wall daily using a standard hoof brush. For general maintenance and conditioning, apply frog, sole and coronary band twice a week. To aid hoof growth apply to coronary band every other day.

Hoof Moisturiser Ingredients Statement. This product contains: Ethyl alcohol CAS No. 64-17-5. Polyethylene glycol CAS No. 25322-68-3. Lauryl oil CAS No. 84603-73-6.

Keep out of reach of children. Keep container tightly closed. Highly flammable liquid and vapour. Keep away from heat, hot surfaces, sparks, open flames and other ignition sources. No smoking. Use only in a well-ventilated area or outdoors. If on skin or hair: Rinse with water/shower. If in eyes: Rinse immediately with plenty of water. Obtain medical attention if pain, blinking or redness persist. Do not eat, drink or smoke during use. Harmful if swallowed. Store in a cool dry place away from animal feedingstuff.

For Equine Use Only

1 Litre

Penleigh Irving Ltd.

Dilton Marsh, Wiltshire, BK13 3SN, UK

+44 (0) 1373 827649 email: info@keratex.com

www.keratex.com